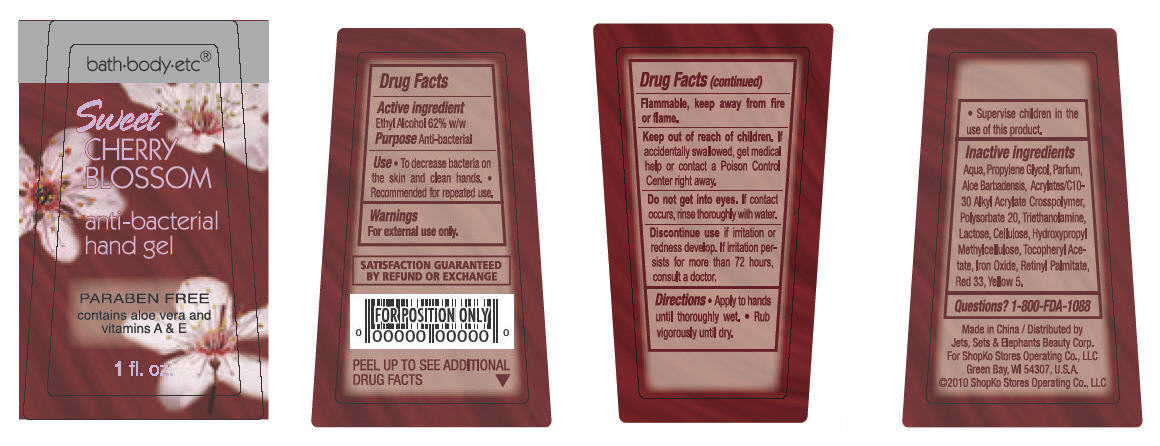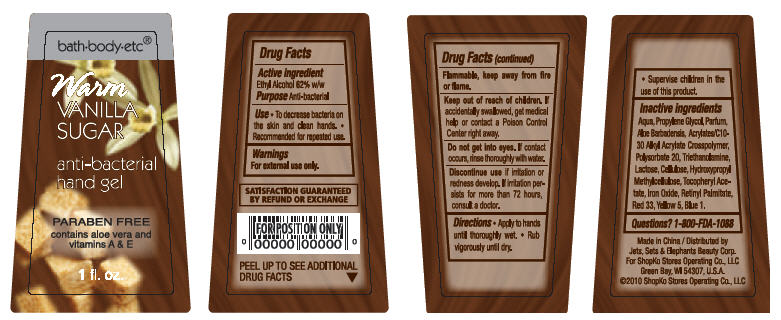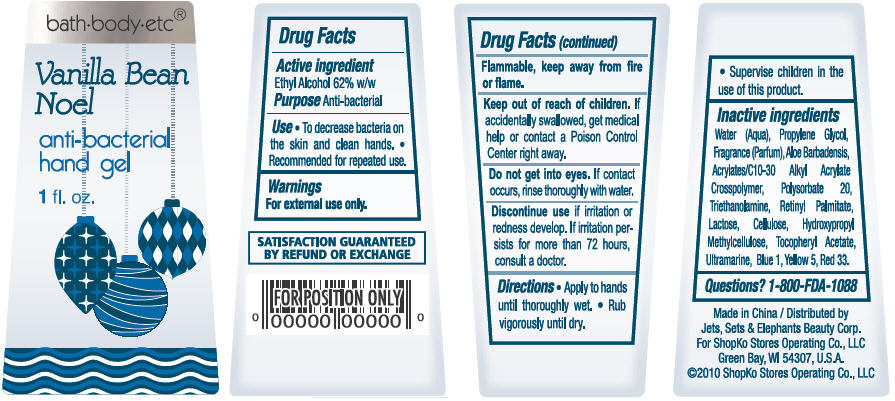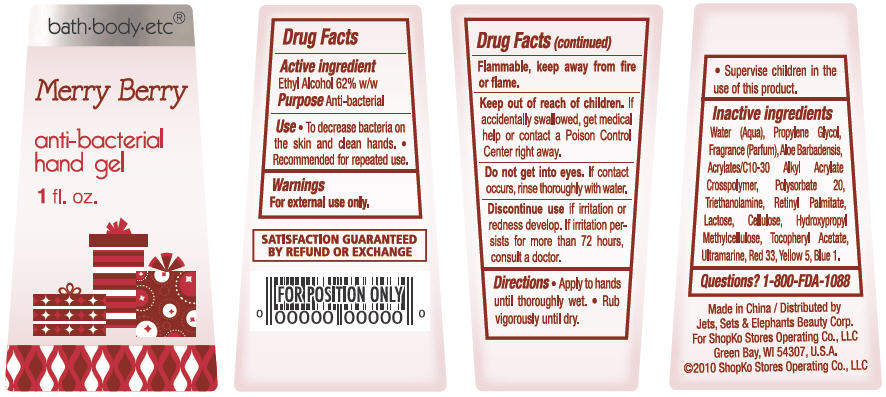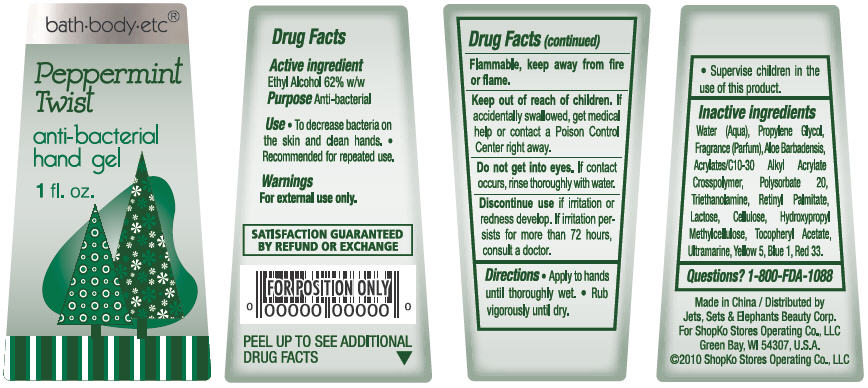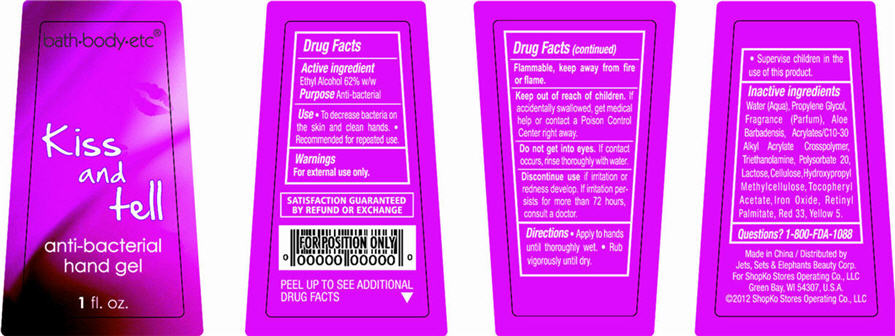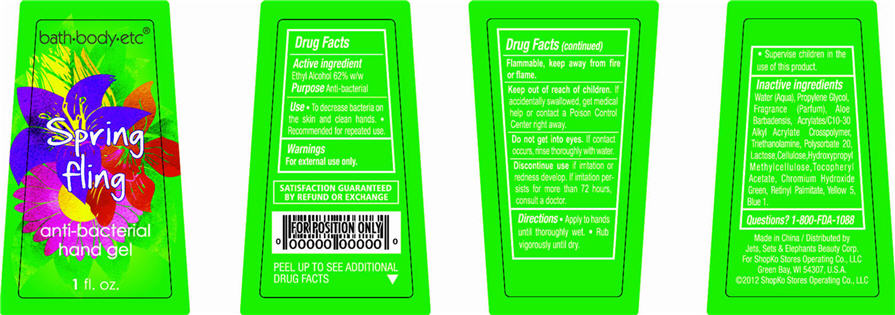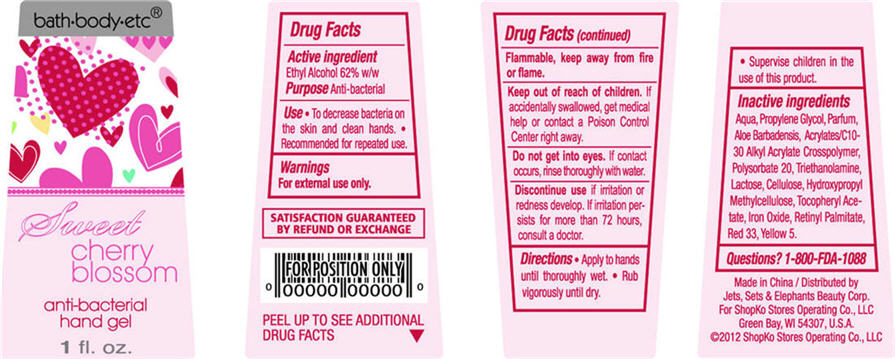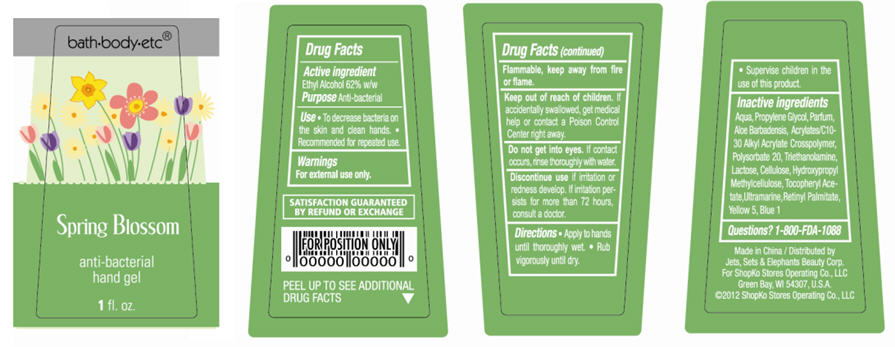 DRUG LABEL: Anti-bacterial Hand
NDC: 50988-270 | Form: GEL
Manufacturer: Jets, Sets, & Elephants Beauty Corp.
Category: otc | Type: HUMAN OTC DRUG LABEL
Date: 20111206

ACTIVE INGREDIENTS: ALCOHOL 18.335 mL/29.574 mL
INACTIVE INGREDIENTS: WATER; PROPYLENE GLYCOL; ALOE VERA LEAF; CARBOMER COPOLYMER TYPE B (ALLYL PENTAERYTHRITOL CROSSLINKED); POLYSORBATE 20; TROLAMINE; LACTOSE; .ALPHA.-TOCOPHEROL ACETATE, D-; FERRIC OXIDE RED; VITAMIN A PALMITATE; D&C RED NO. 33; FD&C YELLOW NO. 5

bath-body-etc® anti-bacterial hand gel - Sweet Cherry Blossom, Warm Vanilla Sugar, Vanilla Bean Noel, Merry Berry, Peppermint Twist,
Kiss and Tell, Spring Fling, Sweet Cherry Blossom, Spring Blossom

ACTIVE INGREDIENT

Ethyl Alcohol 62% w/w

PURPOSE

Anti-bacterial

USE

- To decrease bacteria on the skin and clean hands.
- Recommended for repeated use.

WARNINGS

For external use only. Flammable, keep away from fire or flame.

Keep out of reach of children.

If accidentally swallowed, get medical help or contact a Poison Control Center right away.

Do not get into eyes.

If contact occurs, rinse thoroughly with water.

Discontinue use

if irritation or redness develop. If irritation persists for more than 72 hours, consult a doctor.

DIRECTIONS

- Apply to hands until thoroughly wet.
- Rub vigorously until dry.
- Supervise children in the use of this product.

Inactive Ingredients

Sweet Cherry Blossom

Water, Propylene Glycol, Parfum, Aloe Barbadensis, Acrylates/C10-30 Alkyl Acrylate Crosspolymer, Polysorbate 20, Triethanolamine, Lactose, Cellulose, Hydroxypropyl Methylcellulose, Tocopheryl Acetate, Iron Oxide, Retinyl Palmitate, Red 33, Yellow 5

Warm Vanilla Sugar

Water, Propylene Glycol, Parfum, Aloe Barbadensis, Acrylates/C10-30 Alkyl Acrylate Crosspolymer, Polysorbate 20, Triethanolamine, Lactose, Cellulose, Hydroxypropyl Methylcellulose, Tocopheryl Acetate, Iron Oxide, Retinyl Palmitate, Red 33, Yellow 5, Blue 1

Vanilla Bean Noel

Water, Propylene Glycol, Parfum, Aloe Barbadensis, Acrylates/C10-30 Alkyl Acrylate Crosspolymer, Polysorbate 20, Triethanolamine, Lactose, Cellulose, Hydroxypropyl Methylcellulose, Tocopheryl Acetate, Retinyl Palmitate, Ultramarine, Red 33, Yellow 5, Blue 1

Merry Berry

Water, Propylene Glycol, Parfum, Aloe Barbadensis, Acrylates/C10-30 Alkyl Acrylate Crosspolymer, Polysorbate 20, Triethanolamine, Lactose, Cellulose, Hydroxypropyl Methylcellulose, Tocopheryl Acetate, Retinyl Palmitate, Ultramarine, Red 33, Yellow 5, Blue 1

Peppermint Twist

Water, Propylene Glycol, Parfum, Aloe Barbadensis, Acrylates/C10-30 Alkyl Acrylate Crosspolymer, Polysorbate 20, Triethanolamine, Lactose, Cellulose, Hydroxypropyl Methylcellulose, Tocopheryl Acetate, Retinyl Palmitate, Ultramarine, Red 33, Yellow 5, Blue 1

Kiss and Tell

Water, Propylene Glycol, Parfum, Aloe Barbadensis, Acrylates/C10-30 Alkyl Acrylate Crosspolymer, Triethanolamine, Polysorbate 20, Lactose, Cellulose, Hydroxypropyl Methylcellulose, Tocopheryl Acetate, Iron Oxide, Retinyl Palmitate, Red 33, Yellow 5

Spring Fling

Water, Propylene Glycol, Parfum, Aloe Barbadensis, Acrylates/C10-30 Alkyl Acrylate Crosspolymer, Triethanolamine, Polysorbate 20, Lactose, Cellulose, Hydroxypropyl Methylcellulose, Tocopheryl Acetate, Chromium Hydroxide Green, Retinyl Palmitate, Yellow 5, Blue 1

Sweet Cherry Blossom

Water, Propylene Glycol, Parfum, Aloe Barbadensis, Acrylates/C10-30 Alkyl Acrylate Crosspolymer, Polysorbate 20, Triethanolamine, Lactose, Cellulose, Hydroxypropyl Methylcellulose, Tocopheryl Acetate, Iron Oxide, Retinyl Palmitate, Red 33, Yellow 5

Spring Blossom

Water, Propylene Glycol, Parfum, Aloe Barbadensis, Acrylates/C10-30 Alkyl Acrylate Crosspolymer, Polysorbate 20, Triethanolamine, Lactose, Cellulose, Hydroxypropyl Methylcellulose, Tocopheryl Acetate, Ultramarine, Retinyl Palmitate, Yellow 5, Blue 1

QUESTIONS?

1-800-FDA-1088

Made in China

Distributed by Jets, Sets & Elephants Beauty Corp.

For ShopKo Stores Operating Co., LLC

Green Bay, WI 54307, U.S.A

©2010 ShopKo Stores Operating Co., LLC

PACKAGE/LABEL PRINCIPAL DISPLAY PANEL - BOTTLE LABEL

bath-body-etc®

Sweet Cherry Blossom

anti-bacterial

hand gel

PARABEN FREE

contains aloe vera and

vitamins A & E

1 fl oz

Sweet Cherry Blossom Bottle Label

PACKAGE/LABEL PRINCIPAL DISPLAY PANEL - BOTTLE LABEL

bath-body-etc®

Warm Vanilla Sugar

anti-bacterial

hand gel

PARABEN FREE

contains aloe vera and

vitamins A & E

1 fl oz

Warm Vanilla Sugar Bottle Label

PACKAGE/LABEL PRINCIPAL DISPLAY PANEL - BOTTLE LABEL

bath-body-etc®

Vanilla Bean Noel

anti-bacterial

hand gel

1 fl oz

Vanilla Bean Noel Bottle Label

PACKAGE/LABEL PRINCIPAL DISPLAY PANEL - BOTTLE LABEL

bath-body-etc®

Merry Berry

anti-bacterial

hand gel

1 fl oz

Merry Berry Bottle Label

PACKAGE/LABEL PRINCIPAL DISPLAY PANEL - BOTTLE LABEL

bath-body-etc®

Peppermint Twist

anti-bacterial

hand gel

1 fl oz

Peppermint Twist Bottle Label

PACKAGE/LABEL PRINCIPAL DISPLAY PANEL - BOTTLE LABEL

bath-body-etc®

Kiss and tell

anti-bacterial

hand gel

1 fl oz

Kiss and tell Bottle Label

PACKAGE/LABEL PRINCIPAL DISPLAY PANEL - BOTTLE LABEL

bath-body-etc®

Spring fling

anti-bacterial

hand gel

1 fl oz

Spring fling Bottle Label

PACKAGE/LABEL PRINCIPAL DISPLAY PANEL - BOTTLE LABEL

bath-body-etc®

Sweet cherry blossom

anti-bacterial

hand gel

1 fl oz

Sweet cherry blossom Bottle Label

PACKAGE/LABEL PRINCIPAL DISPLAY PANEL - BOTTLE LABEL

bath-body-etc®

Spring Blossom

anti-bacterial

hand gel

1 fl oz

Spring Blossom Bottle Label